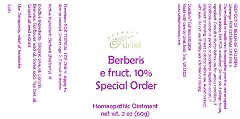 DRUG LABEL: Berberis e fruct. 10% Special Order
NDC: 48951-2037 | Form: OINTMENT
Manufacturer: Uriel Pharmacy Inc.
Category: homeopathic | Type: HUMAN OTC DRUG LABEL
Date: 20190611

ACTIVE INGREDIENTS: BERBERIS VULGARIS ROOT BARK 1 [hp_X]/1 g
INACTIVE INGREDIENTS: TEA TREE OIL; OLIVE OIL; LANOLIN; YELLOW WAX; CITRUS PARADISI SEED; SUNFLOWER OIL; SORBIC ACID

Berberis e fruct. 10% Special Order

INDICATIONS AND USAGE

Directions: FOR TOPICAL USE ONLY.

DOSAGE AND ADMINISTRATION

Apply to skin as needed. Under age 2: Consult a doctor.

Active Ingredient: Berberis (Barberry) 1X

INACTIVE INGREDIENT

Inactive Ingredients: Organic olive oil, Lanolin, Beeswax, Sunflower seed oil, Sorbic acid, Tea tree oil, Grapefruit seed extract

PURPOSE

Use: Temporary relief of headache.

KEEP OUT OF REACH OF CHILDREN.

Warnings: FOR EXTERNAL USE ONLY.
Claims based on traditional homeopathic practice, not accepted medical evidence. Not FDA evaluated. Do not use if allergic to any ingredient. Consult a doctor before use for serious conditions, if conditions worsen or persist, or accidental ingestion occurs. If pregnant or nursing, consult a doctor before use. Avoid contact with eyes. Do not use if safety seal is broken or missing.

Questions? Call 866.642.2858
Made with care by Uriel, East Troy, WI 53120
www.urielpharmacy.com